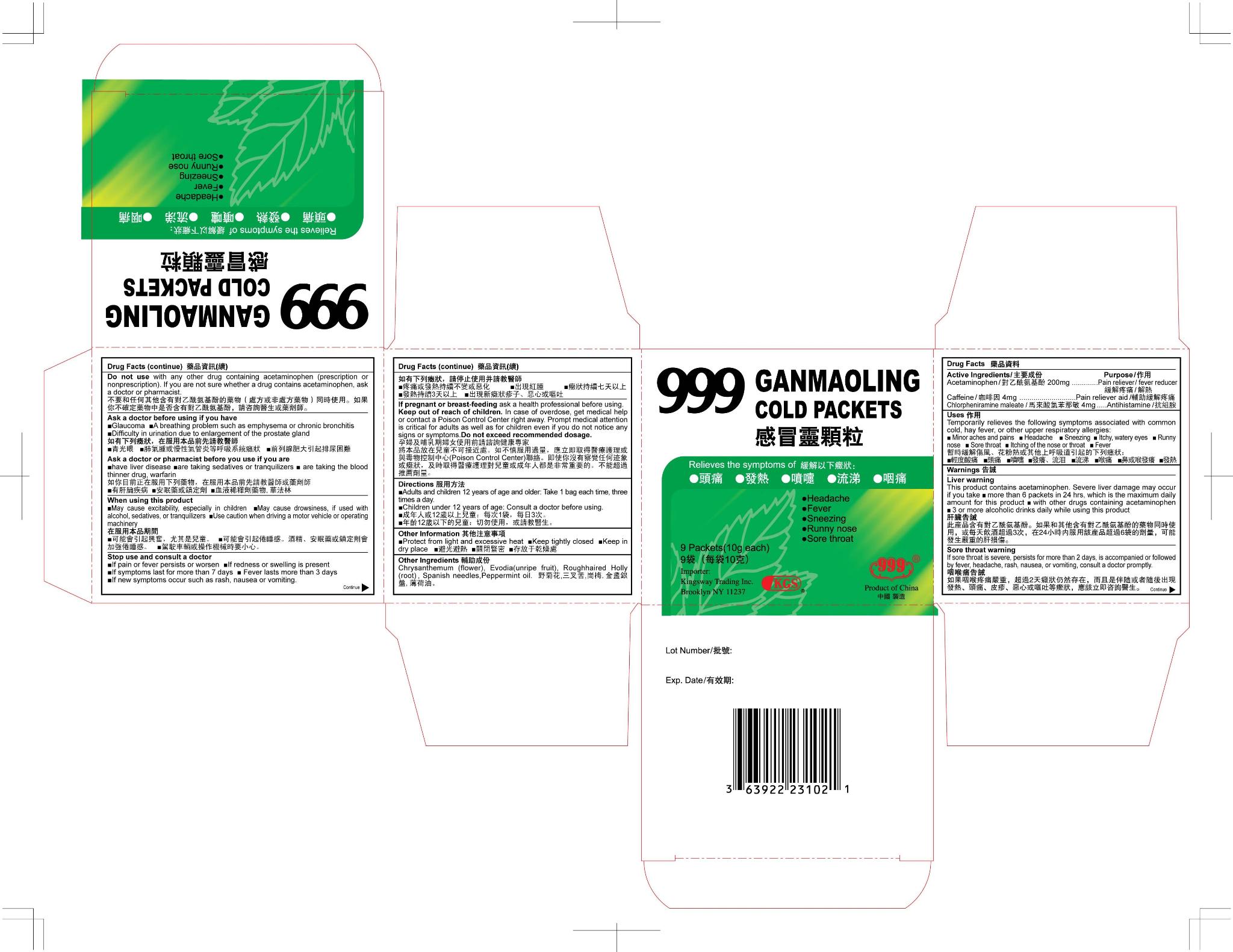 DRUG LABEL: Ganmaoling
NDC: 63922-600 | Form: GRANULE
Manufacturer: Kingsway Trading
Category: otc | Type: HUMAN OTC DRUG LABEL
Date: 20120613

ACTIVE INGREDIENTS: ACETAMINOPHEN 200 mg/1 1; CAFFEINE 4 mg/1 1; CHLORPHENIRAMINE MALEATE 4 mg/1 1
INACTIVE INGREDIENTS: DENDRANTHEMA INDICUM FLOWER; TETRADIUM RUTICARPUM FRUIT; BIDENS BIPINNATA TOP; PEPPERMINT OIL

Drug Facts

Active Ingredients
Acetaminophen 200 mg
Caffeine 4mg
Chlorpheniramine Maleate 4 mg

Purpose
Pain reliever/fever reducer
Pain reliever aid
Antihistamine

Uses
Temporarily relieves the following symptoms associated with common cold, hay fever, or other upper respiratory allergies:
■ Minor aches and pains ■ Headache ■ Sneezing ■ Itchy, watery eyes ■ Runny nose ■ Sore throat ■ Itching of the nose or throat ■ Fever

Warnings
Sore throat warning
If sore throat is severe, persists for more than 2 days, is accompanied or followed by fever, headache, rash, nausea, or vomiting, consult a doctor promptly.
Liver warning
This product contains acetaminophen, Severe liver damage many occur if you take ■ more than 6 packets in 24 hours, which is the maximum daily amount for this product ■with other drugs containing acetaminophen ■3 or more alcoholic drinks daily while using this product.
Do not use with any other drug containing acetaminophen (prescription or nonprescription), if you are not sure whether a drug contains acetaminophen, ask a doctor or pharmacist.

Ask a doctor before use you have
• Glaucoma • A breathing problem such as emphysema or chronic bronchitis • Difficulty in urination due to enlargement of the prostate gland

Ask a doctor or pharmacist before you use if you ■have liver disease ■are taking sedatives or tranquilizers ■ are taking the blood thinner drug, warfarin

When using this product ■ May cause excitability, especially in children ■ May cause drowsiness, if used with alcohol, sedatives, or tranquilizers ■ Use caution when driving a motor vehicle or operating machinery.

Stop use and consult a doctor ■ If pain or fever persists or worsen ■ If redness or swelling is present ■ If symptoms last for more than 7 days ■ Fever lasts more than 3 days ■ If new symptoms occur such as rash, nausea or vomiting.

KEEP OUT OF REACH OF CHILDREN

If pregnant or breast-feeding ask a health professional before using.
Keep out of reach of children. In case of overdose, get medical help or contact a Poison Control Center right away. Prompt medical attention is critical for adults as well as for children even if you do not notice any signs of symptoms. Do not exceed recommended dosage

Directions
■ Adults and children 12 years of age and older: Take 1 packet 3 times a day. Do not exceed 6 packets in 24 hours.
■ Children under 12 years of age: Consult a doctor before using.

Other Information
■ Protect form light and excessive heat ■ Keep tightly closed ■ Keep in dry place

INACTIVE INGREDIENT

Other Ingredients
Chrysanthemum (flower), Evodia (unripe fruit), Roughhaired Holly (root), Spanish needles, Peppermint oil.

Package Label